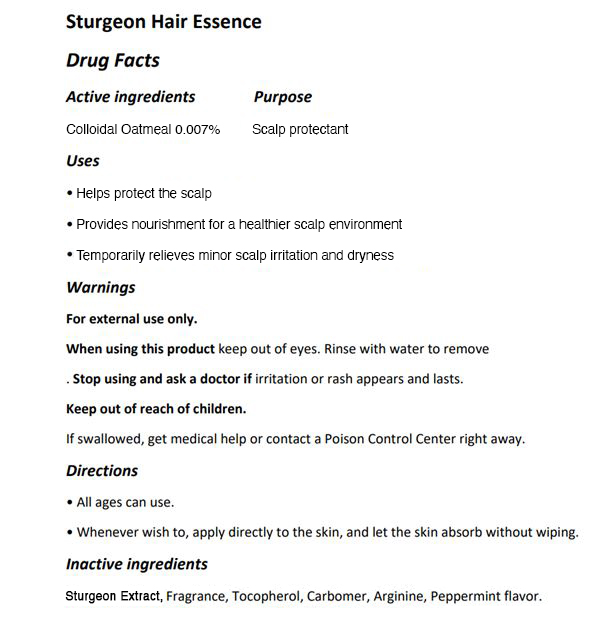 DRUG LABEL: The Zoeun Skin Sturgeon Hair Essence
NDC: 83636-121 | Form: LIQUID
Manufacturer: Sturgeonbio Co.,Ltd.
Category: otc | Type: HUMAN OTC DRUG LABEL
Date: 20251001

ACTIVE INGREDIENTS: OATMEAL 0.007 g/100 mL
INACTIVE INGREDIENTS: CARBOMER HOMOPOLYMER, UNSPECIFIED TYPE; FRAGRANCE 13576; STURGEON, UNSPECIFIED; TOCOPHEROL; ARGININE; PEPPERMINT

121 THE ZOEUN SKIN STURGEON HAIR ESSENCE

Active Ingredients

Colloidal Oatmeal 0.007%

Purpose

Scalp Protectant

Uses

- Helps protect the scalp.
- Provides nourishment for a healthier scalp environment.
- Temporarily relieves minor scalp irritation and dryness.

Warnings

For external use only.

Warnings

- When using this product keep out of eyes.
- Rinse with water to remove.

Warnings

Stop using and ask a doctor if irritation or rash appears and lasts.

Warnings

- Keep out of reach of children.
- If swallowed, get medical help or contact a Poison Control Center right away.

Directions

- All ages can use.
- Whenever wish to, apply directly to the skin, and let the skin absorb without wiping.

Inactive ingredients

Sturgeon Extract, Fragrance, Tocopherol, Carbomer, Arginine, Peppermint flavor.